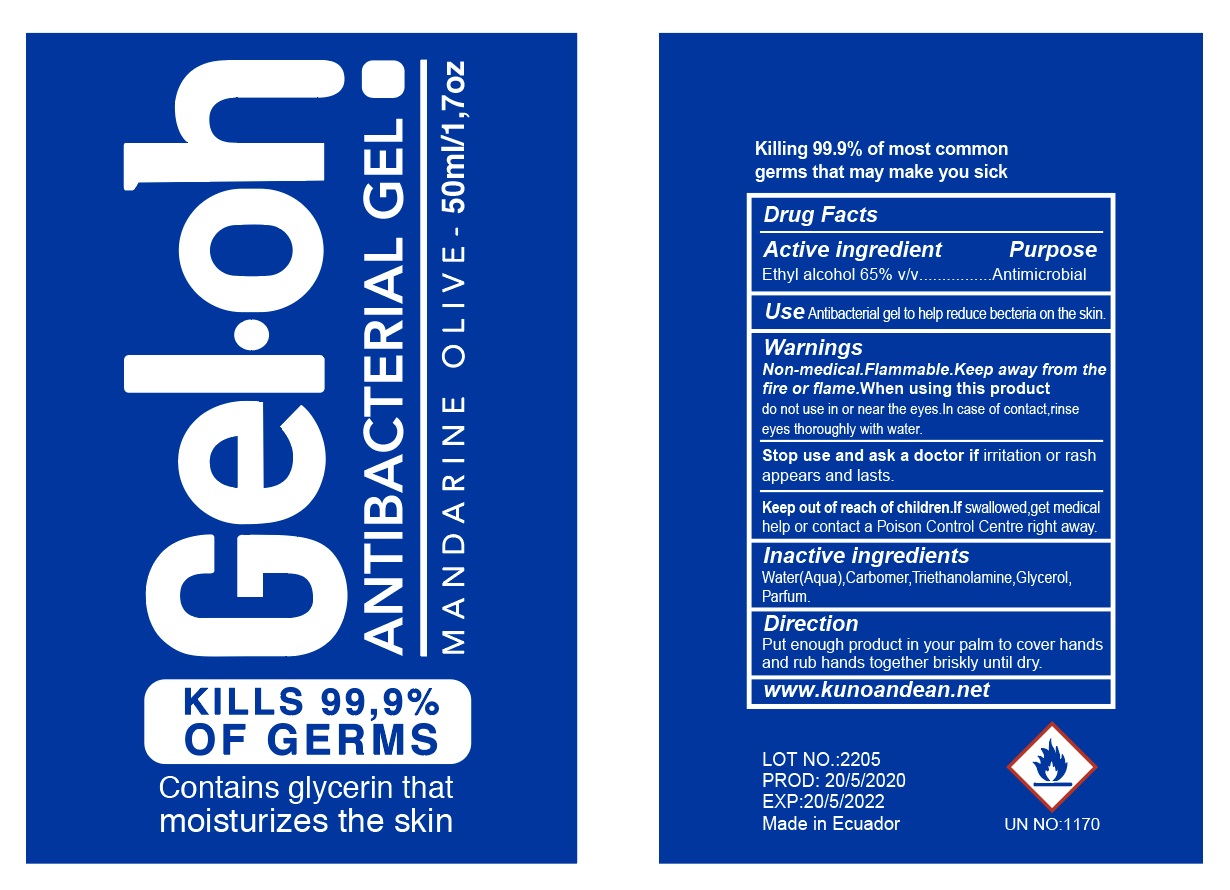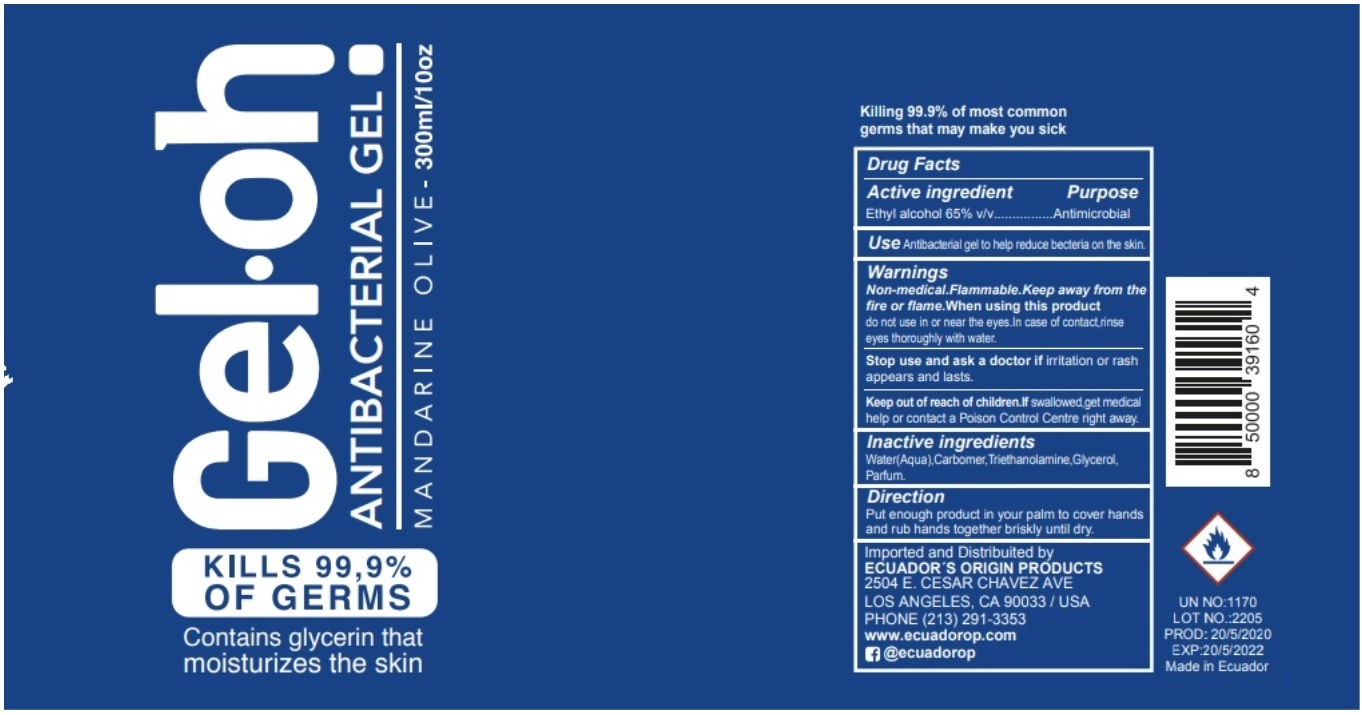 DRUG LABEL: oh Antibacterial Mandarine Olive
NDC: 80073-001 | Form: GEL
Manufacturer: Salgraf Cia Ltda
Category: otc | Type: HUMAN OTC DRUG LABEL
Date: 20201019

ACTIVE INGREDIENTS: ALCOHOL 0.65 mL/1 mL
INACTIVE INGREDIENTS: WATER; CARBOMER HOMOPOLYMER, UNSPECIFIED TYPE; TROLAMINE; GLYCERIN

Gel oh Antibacterial Gel, Mandarine Olive, 65% Ethyl Alcohol

Active ingredient

Ethyl alcohol 65% v/v

Purpose

Antimicrobial

Use

Antibacterial gel to help reduce bacteria on the skin.

Warnings

Non-medical.Flammable. Keep away from the fire or flame.

When using this product

do not use in or near the eyes. In case of contact,rinse eyes thoroughly with water.

Stop use and ask a doctor if

irritation or rash appears and lasts.

Keep out of reach of children.

If swallowed,get medical help or contact a Poison Control Center right away.

Inactive ingredients

Water(Aqua), Carbomer, Triethanolamine, Glycerol, Parfum.

Directions

Put enough product in your palm to cover hands and rub hands together briskly until dry.

QUESTIONS

www.kunoandean.net

Imported and Distributed by

ECUADOR'S ORIGIN PRODUCTS

2504 E. CESAR CHAVEZ AVE

LOS ANGELES,CA 90033 / USA

PHONE (213)291-3353

www.ecuadorop.com

@ecuadorop